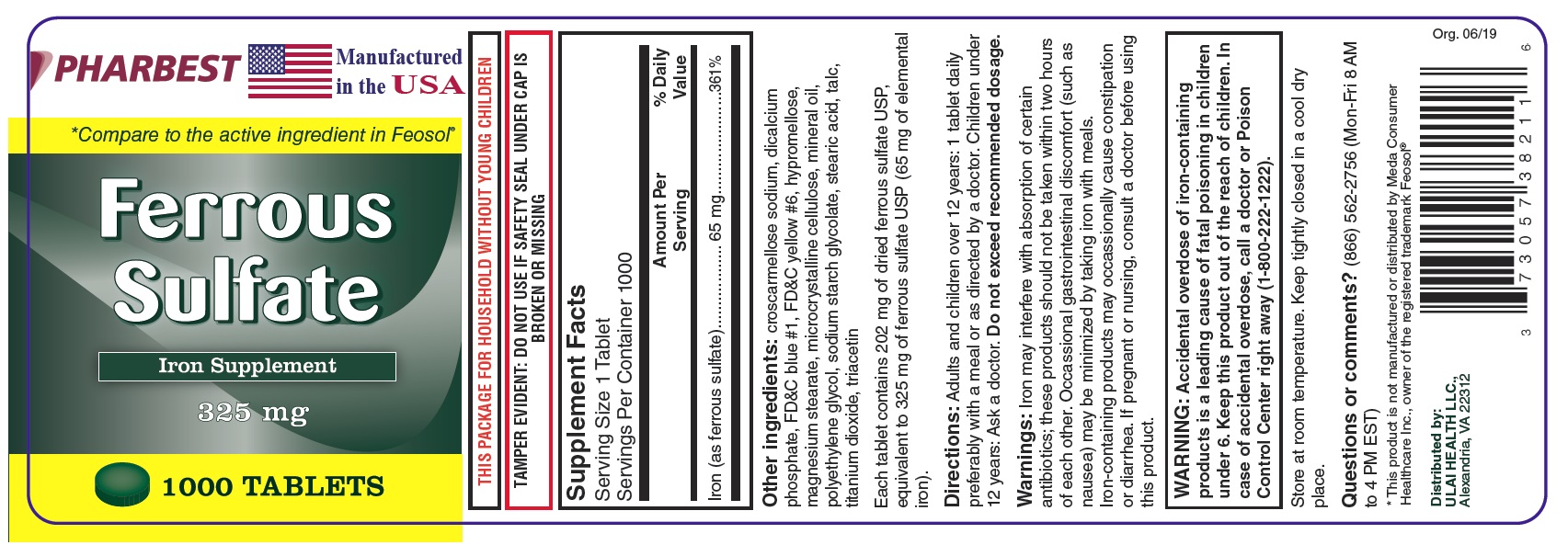 DRUG LABEL: Ferrous Sulfate
NDC: 73057-382 | Form: TABLET, FILM COATED
Manufacturer: Ulai Health LLC
Category: other | Type: DIETARY SUPPLEMENT
Date: 20190723

ACTIVE INGREDIENTS: FERROUS SULFATE 65 mg/1 1
INACTIVE INGREDIENTS: CROSCARMELLOSE SODIUM; CALCIUM PHOSPHATE, DIBASIC, ANHYDROUS; FD&C BLUE NO. 1; FD&C YELLOW NO. 6; HYPROMELLOSE, UNSPECIFIED; MAGNESIUM STEARATE; CELLULOSE, MICROCRYSTALLINE; MINERAL OIL; POLYETHYLENE GLYCOL, UNSPECIFIED; SODIUM STARCH GLYCOLATE TYPE A CORN; STEARIC ACID; TALC; TITANIUM DIOXIDE; TRIACETIN

Supplement Facts

Serving Size 1 Tablet

Servings Per Container 1000

 | Amount Per Serving | % Daily Value
Iron (as ferrous sulfate) | 65 mg | 361%

Other ingredients: croscarmellose sodium, dicalcium phosphate, FD&C blue #1, FD&C yellow #6, hypromellose, magnesium stearate, microcrystalline cellulose, mineral oil, polyethylene glycol, sodium starch glycolate, stearic acid, talc, titanium dioxide, triacetin

Each tablet contains 202 mg of dried ferrous sulfate USP, equivalent to 325 mg of ferrous sulfate USP (65 mg of elemental iron).

Directions:

Adults and children over 12 years: 1 tablet daily preferably with a meal or as directed by a doctor. Children under 12 years: Ask a doctor.

Do not exceed recommended dosage.

Warnings:

Iron may interfere with absorption of certain antibiotics; these products should not be taken within two hours of each other. Occassional gastrointestinal discomfort (such as nausea) may be minimized by taking iron with meals. Iron-containing products may occassionally cause constipation or diarrhea.

If pregnant or nursing, consult a doctor before using this product.

WARNING: Accidental overdose of iron-containing products is a leading cause of fatal poisoning in children under 6. Keep this product out of the reach of children. In case of overdose, call a doctor or Poison Control Center right away (1-800-222-1222).

SAFE HANDLING WARNING

Store at room temperature. Keep tightly closed in a cool dry place.

Questions or comments? (866) 562-2756 (Mon-Fri 8 AM to 4 PM EST)

PACKAGE LABEL

PHARBEST

Manufactured in the USA

*Compare to the active ingredient in Feosol®

Ferrous

Sulfate

Iron Supplement

325 mg

1000 TABLETS